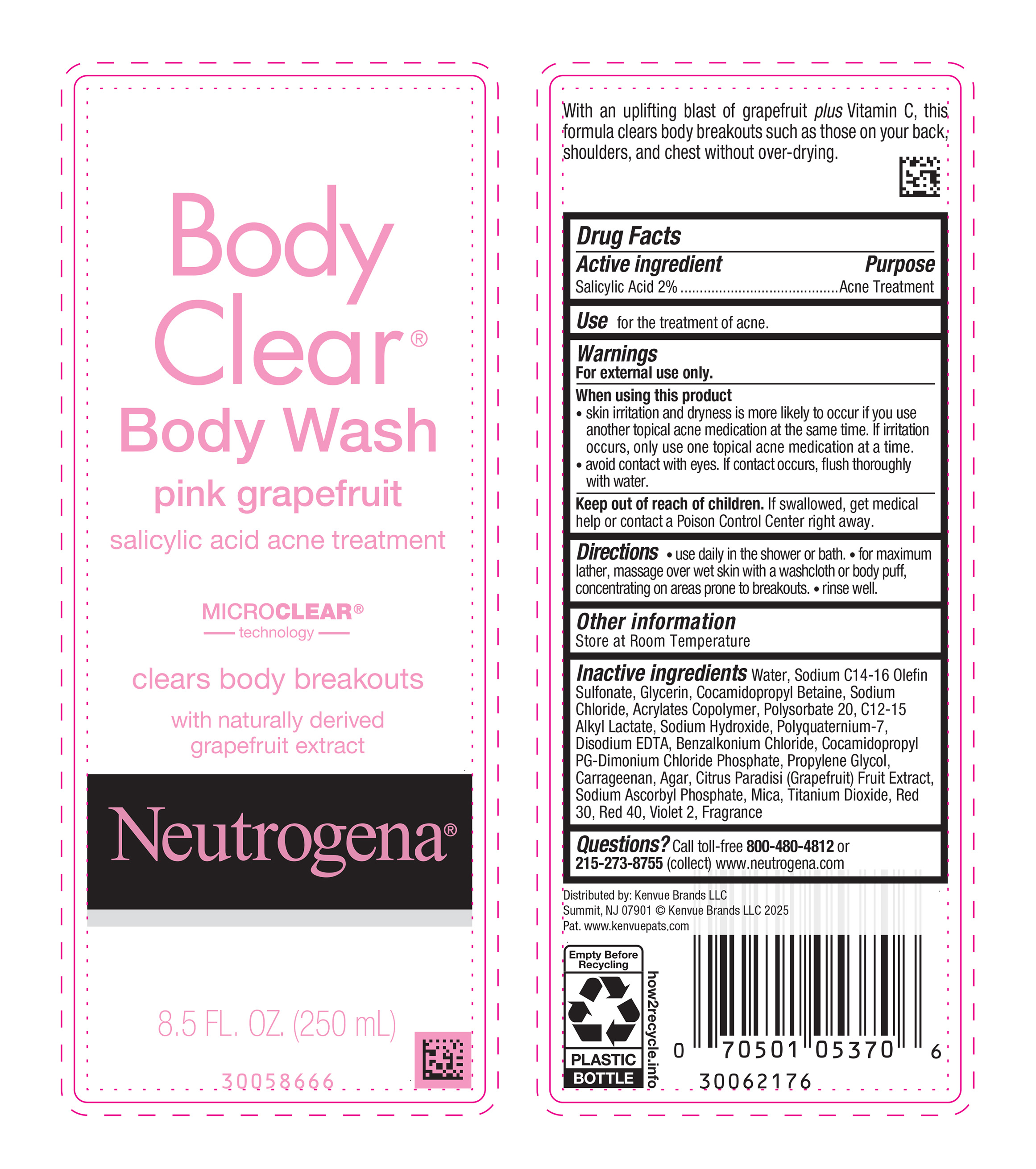 DRUG LABEL: Neutrogena Body Clear Body Wash Pink Grapefruit
NDC: 69968-0910 | Form: LIQUID
Manufacturer: Kenvue Brands LLC
Category: otc | Type: HUMAN OTC DRUG LABEL
Date: 20250820

ACTIVE INGREDIENTS: SALICYLIC ACID 20 mg/1 mL
INACTIVE INGREDIENTS: GRAPEFRUIT; WATER; SODIUM C14-16 OLEFIN SULFONATE; GLYCERIN; COCAMIDOPROPYL BETAINE; SODIUM CHLORIDE; METHACRYLIC ACID - ETHYL ACRYLATE COPOLYMER (4500 MPA.S); POLYSORBATE 20; C12-15 ALKYL LACTATE; SODIUM HYDROXIDE; EDETATE DISODIUM; BENZALKONIUM CHLORIDE; POLYQUATERNIUM-7 (70/30 ACRYLAMIDE/DADMAC; 1600000 MW); COCAMIDOPROPYL PROPYLENE GLYCOL-DIMONIUM CHLORIDE PHOSPHATE; PROPYLENE GLYCOL; CARRAGEENAN; AGAR, UNSPECIFIED; MICA; TITANIUM DIOXIDE; D&C RED NO. 30; FD&C RED NO. 40; D&C VIOLET NO. 2; SODIUM ASCORBYL PHOSPHATE

Neutrogena Body Clear Body Wash Pink Grapefruit

Drug Facts

Active ingredient

Salicylic Acid 2%

Purpose

Acne Treatment

Use

for the treatment of acne.

Warnings

For external use only.

When using this product

- skin irritation and dryness is more likely to occur if you use another topical acne medication at the same time. If irritation occurs, only use one topical acne medication at a time.
- avoid contact with eyes. If contact occurs, flush thoroughly with water.

Keep out of reach of children. If swallowed, get medical help or contact a Poison Control Center right away.

Directions

- use daily in the shower or bath.
- for maximum lather, massage over wet skin with a washcloth or body puff, concentrating on areas prone to breakouts.
- rinse well.

Other information

Store at Room Temperature

Inactive ingredients

Water, Sodium C14-16 Olefin Sulfonate, Glycerin, Cocamidopropyl Betaine, Sodium Chloride, Acrylates Copolymer, Polysorbate 20, C12-15 Alkyl Lactate, Sodium Hydroxide, Polyquaternium-7, Disodium EDTA, Benzalkonium Chloride, Cocamidopropyl PG-Dimonium Chloride Phosphate, Propylene Glycol, Carrageenan, Agar, Citrus Paradisi (Grapefruit) Fruit Extract, Sodium Ascorbyl Phosphate, Mica, Titanium Dioxide, Red 30, Red 40, Violet 2, Fragrance

Questions?

Call toll-free 800-480-4812 or 215-273-8755 (collect) www.neutrogena.com

Distributed by:

Kenvue Brands LLC
Summit, NJ 07901

PRINCIPAL DISPLAY PANEL - 250 mL Bottle Label

Body

Clear®

Body Wash

pink grapefruit

salicylic acid acne treatment

MICRO CLEAR®

technology

clears body breakouts

with naturally derived

grapefruit extract

Neutrogena®

8.5 FL. OZ. (250mL)